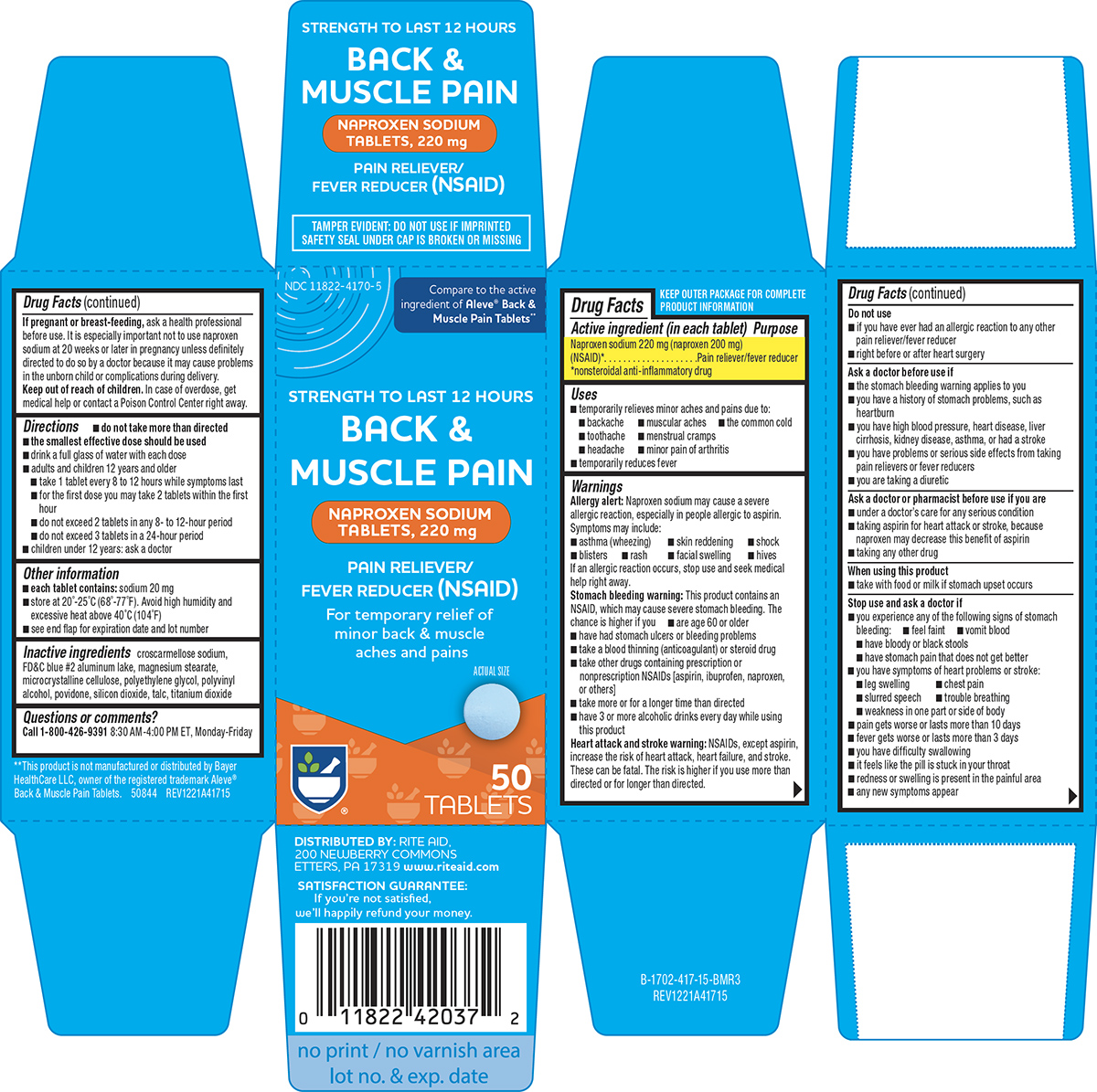 DRUG LABEL: Back and Muscle Pain
NDC: 11822-4170 | Form: TABLET, FILM COATED
Manufacturer: Rite Aid Corporation
Category: otc | Type: HUMAN OTC DRUG LABEL
Date: 20260211

ACTIVE INGREDIENTS: NAPROXEN SODIUM 220 mg/1 1
INACTIVE INGREDIENTS: CROSCARMELLOSE SODIUM; FD&C BLUE NO. 2 ALUMINUM LAKE; MAGNESIUM STEARATE; MICROCRYSTALLINE CELLULOSE; POLYETHYLENE GLYCOL, UNSPECIFIED; POLYVINYL ALCOHOL, UNSPECIFIED; POVIDONE, UNSPECIFIED; SILICON DIOXIDE; TALC; TITANIUM DIOXIDE

Rite Aid 44-417 BM

Active ingredient (in each tablet)

Naproxen sodium 220 mg (naproxen 200 mg) (NSAID)*
*nonsteroidal anti-inflammatory drug

Purpose

Pain reliever/fever reducer

Uses

- temporarily relieves minor aches and pains due to:
  - backache
  - muscular aches
  - the common cold
  - toothache
  - menstrual cramps
  - headache
  - minor pain of arthritis
- temporarily reduces fever

Warnings

Allergy alert: Naproxen sodium may cause a severe allergic reaction, especially in people allergic to aspirin. Symptoms may include:

- asthma (wheezing)
- skin reddening
- shock
- blisters
- rash
- facial swelling
- hives

If an allergic reaction occurs, stop use and seek medical help right away.

Stomach bleeding warning: This product contains an NSAID, which may cause severe stomach bleeding. The chance is higher if you

- are age 60 or older
- have had stomach ulcers or bleeding problems
- take a blood thinning (anticoagulant) or steroid drug
- take other drugs containing prescription or nonprescription NSAIDs [aspirin, ibuprofen, naproxen, or others]
- take more or for a longer time than directed
- have 3 or more alcoholic drinks every day while using this product

Heart attack and stroke warning: NSAIDs, except aspirin, increase the risk of heart attack, heart failure, and stroke. These can be fatal. The risk is higher if you use more than directed or for longer than directed.

Do not use

- if you have ever had an allergic reaction to any other pain reliever/fever reducer
- right before or after heart surgery

Ask a doctor before use if

- the stomach bleeding warning applies to you
- you have a history of stomach problems, such as heartburn
- you have high blood pressure, heart disease, liver cirrhosis, kidney disease, asthma, or had a stroke
- you have problems or serious side effects from taking pain relievers or fever reducers
- you are taking a diuretic

Ask a doctor or pharmacist before use if you are

- under a doctor’s care for any serious condition
- taking aspirin for heart attack or stroke, because naproxen may decrease this benefit of aspirin
- taking any other drug

When using this product

- take with food or milk if stomach upset occurs

Stop use and ask a doctor if

- you experience any of the following signs of stomach bleeding:
  - feel faint
  - vomit blood
  - have bloody or black stools
  - have stomach pain that does not get better
- you have symptoms of heart problems or stroke:
  - leg swelling
  - chest pain
  - slurred speech
  - trouble breathing
  - weakness in one part or side of body
- pain gets worse or lasts more than 10 days
- fever gets worse or lasts more than 3 days
- you have difficulty swallowing
- it feels like the pill is stuck in your throat
- redness or swelling is present in the painful area
- any new symptoms appear

If pregnant or breast-feeding,

ask a health professional before use. It is especially important not to use naproxen sodium at 20 weeks or later in pregnancy unless definitely directed to do so by a doctor because it may cause problems in the unborn child or complications during delivery.

Keep out of reach of children.

In case of overdose, get medical help or contact a Poison Control Center right away.

Directions

- do not take more than directed
- the smallest effective dose should be used
- drink a full glass of water with each dose
- adults and children 12 years and older
  - take 1 tablet every 8 to 12 hours while symptoms last
  - for the first dose you may take 2 tablets within the first hour
  - do not exceed 2 tablets in any 8- to 12-hour period
  - do not exceed 3 tablets in a 24-hour period
- children under 12 years: ask a doctor

Other information

- each tablet contains: sodium 20 mg
- store at 20°-25°C (68°-77°F). Avoid high humidity and excessive heat above 40°C (104°F)
- see end flap for expiration date and lot number

Inactive ingredients

croscarmellose sodium, FD&C blue #2 aluminum lake, magnesium stearate, microcrystalline cellulose, polyethylene glycol, polyvinyl alcohol, povidone, silicon dioxide, talc, titanium dioxide

Questions or comments?

Call 1-800-426-9391 8:30 AM-4:00 PM ET, Monday-Friday

Principal display panel

NDC 11822-4170-5

Compare to the active
ingredient of Aleve® Back &
Muscle Pain Tablets**

STRENGTH TO LAST 12 HOURS

BACK &
MUSCLE PAIN

NAPROXEN SODIUM
TABLETS, 220 mg

PAIN RELIEVER/
FEVER REDUCER (NSAID)

For temporary relief of
minor back & muscle
aches and pains

ACTUAL SIZE

50
TABLETS

TAMPER EVIDENT: DO NOT USE IF IMPRINTED
SAFETY SEAL UNDER CAP IS BROKEN OR MISSING

DISTRIBUTED BY: RITE AID,
200 NEWBERRY COMMONS
ETTERS, PA 17319 www.riteaid.com

SATISFACTION GUARANTEE:
If you’re not satisfied,
we’ll happily refund your money.

**This product is not manufactured or distributed by Bayer
HealthCare LLC, owner of the registered trademark Aleve®
Back & Muscle Pain Tablets. 50844 REV1221A41715

Rite Aid 44-417 BM